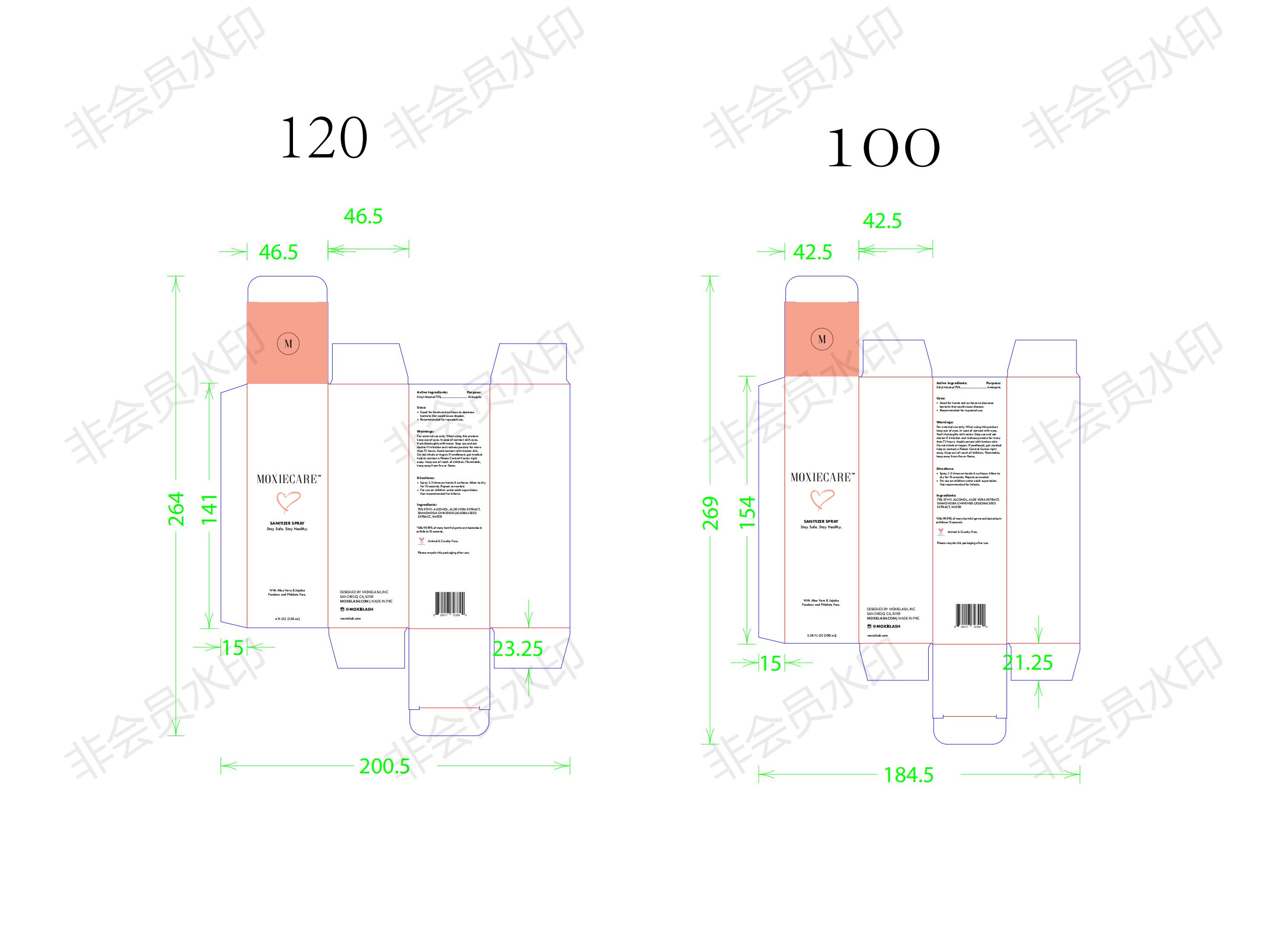 DRUG LABEL: Moxiecare SanitizerSpray
NDC: 75375-006 | Form: SPRAY
Manufacturer: Guangzhou Tongzi Biological Technology Co., Ltd
Category: otc | Type: HUMAN OTC DRUG LABEL
Date: 20200430

ACTIVE INGREDIENTS: ALCOHOL 75 mL/100 mL
INACTIVE INGREDIENTS: ALOE VERA LEAF; SIMMONDSIA CHINENSIS SEED; WATER

Active Ingredient(s)

Alcohol 75%

Purpose

Antiseptic

Use

Good for hand and surfaces to decrease bacteria that could cause disease.Recommended for repeated use.

Warnings

For external use only. When using this product keep out of eyes. In case of contact with eyes,flflush thoroughly with water. Stop use and ask doctor if irritation and redness persists for more than 72 hours. Avoid contact with broken skin.Do not inhale or ingest. If swallowed, get medical help or contact a Poison Control Center right away. Keep out of reach of children. Flammable,keep away from fifire or flflame.

Do not use

- in children less than 2 months of age
- on open skin wounds

When using this product keep out of eyes, ears, and mouth. In case of contact with eyes, rinse eyes thoroughly with water.
Stop use and ask a doctor if irritation or rash occurs. These may be signs of a serious condition.
Keep out of reach of children. If swallowed, get medical help or contact a Poison Control Center right away.

Stop use and ask a doctor if irritation or rash occurs. These may be signs of a serious condition.

Keep out of reach of children. If swallowed, get medical help or contact a Poison Control Center right away.

Directions

Spray 2-3 times on hands & surfaces. Allow to dry for 15 seconds. Repeat as needed.For use on children under adult supervision.Not recommended for infants.

Other information

- Store between 15-30C (59-86F)
- Avoid freezing and excessive heat above 40C (104F)

Inactive ingredients

SIMMONDSIA CHINENSIS SEED,ALOE VERA LEAF,WATER.